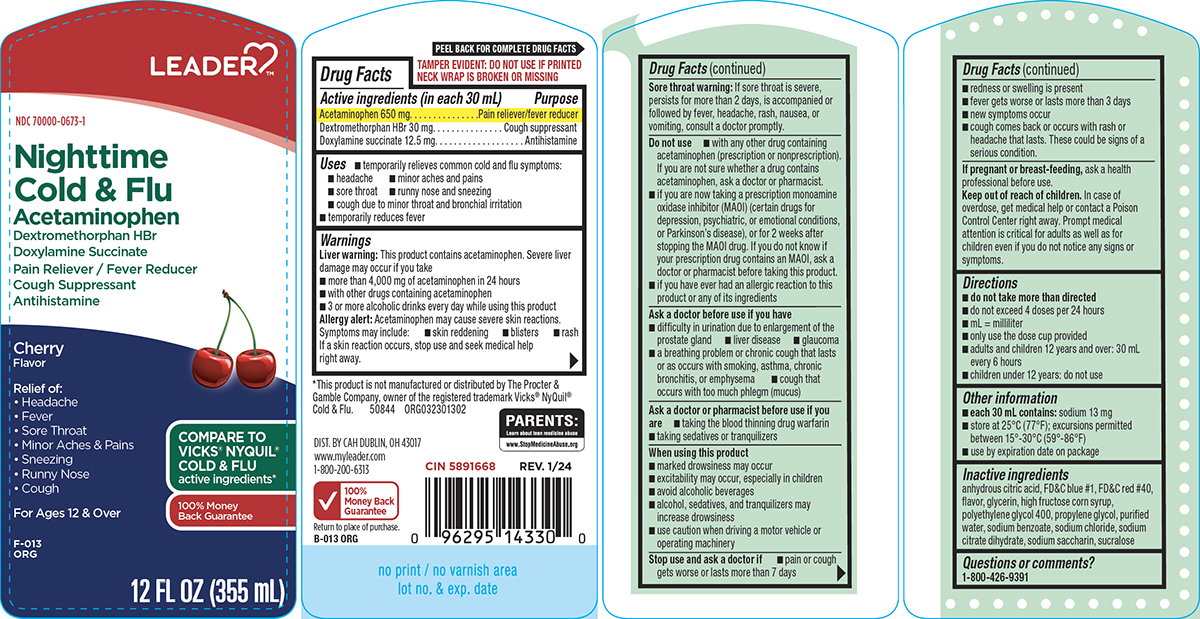 DRUG LABEL: Cold and Flu
NDC: 70000-0673 | Form: SOLUTION
Manufacturer: Cardinal Health 110, LLC. DBA Leader
Category: otc | Type: HUMAN OTC DRUG LABEL
Date: 20250813

ACTIVE INGREDIENTS: ACETAMINOPHEN 650 mg/30 mL; DEXTROMETHORPHAN HYDROBROMIDE 30 mg/30 mL; DOXYLAMINE SUCCINATE 12.5 mg/30 mL
INACTIVE INGREDIENTS: ANHYDROUS CITRIC ACID; FD&C BLUE NO. 1; FD&C RED NO. 40; GLYCERIN; HIGH FRUCTOSE CORN SYRUP; POLYETHYLENE GLYCOL 400; PROPYLENE GLYCOL; WATER; SODIUM BENZOATE; SODIUM CHLORIDE; TRISODIUM CITRATE DIHYDRATE; SACCHARIN SODIUM; SUCRALOSE

Leader 44-013

Active ingredients (in each 30 mL)

Acetaminophen 650 mg
Dextromethorphan HBr 30 mg
Doxylamine succinate 12.5 mg

Purpose

Pain reliever/fever reducer
Cough suppressant
Antihistamine

Uses

- temporarily relieves common cold and flu symptoms:
  - headache
  - minor aches and pains
  - sore throat
  - runny nose and sneezing
  - cough due to minor throat and bronchial irritation
- temporarily reduces fever

Warnings

Liver warning: This product contains acetaminophen. Severe liver damage may occur if you take

- more than 4,000 mg of acetaminophen in 24 hours
- with other drugs containing acetaminophen
- 3 or more alcoholic drinks every day while using this product

Allergy alert: Acetaminophen may cause severe skin reactions. Symptoms may include:

- skin reddening
- blisters
- rash

If a skin reaction occurs, stop use and seek medical help right away.

Sore throat warning: If sore throat is severe, persists for more than 2 days, is accompanied or followed by fever, headache, rash, nausea, or vomiting, consult a doctor promptly.

Do not use

- with any other drug containing acetaminophen (prescription or nonprescription). If you are not sure whether a drug contains acetaminophen, ask a doctor or pharmacist.
- if you are now taking a prescription monoamine oxidase inhibitor (MAOI) (certain drugs for depression, psychiatric, or emotional conditions, or Parkinson’s disease), or for 2 weeks after stopping the MAOI drug. If you do not know if your prescription drug contains an MAOI, ask a doctor or pharmacist before taking this product.
- if you have ever had an allergic reaction to this product or any of its ingredients

Ask a doctor before use if you have

- difficulty in urination due to enlargement of the prostate gland
- liver disease
- glaucoma
- a breathing problem or chronic cough that lasts or as occurs with smoking, asthma, chronic bronchitis, or emphysema
- cough that occurs with too much phlegm (mucus)

Ask a doctor or pharmacist before use if you are

- taking the blood thinning drug warfarin
- taking sedatives or tranquilizers

When using this product

- marked drowsiness may occur
- excitability may occur, especially in children
- avoid alcoholic beverages
- alcohol, sedatives, and tranquilizers may increase drowsiness
- use caution when driving a motor vehicle or operating machinery

Stop use and ask a doctor if

- pain or cough gets worse or lasts more than 7 days
- redness or swelling is present
- fever gets worse or lasts more than 3 days
- new symptoms occur
- cough comes back or occurs with rash or headache that lasts. These could be signs of a serious condition.

If pregnant or breast-feeding,

ask a health professional before use.

Keep out of reach of children.

In case of overdose, get medical help or contact a Poison Control Center right away. Prompt medical attention is critical for adults as well as for children even if you do not notice any signs or symptoms.

Directions

- do not take more than directed
- do not exceed 4 doses per 24 hours
- mL = milliliter
- only use the dose cup provided
- adults and children 12 years and over: 30 mL every 6 hours
- children under 12 years: do not use

Other information

- each 30 mL contains: sodium 13 mg
- store at 25°C (77°F); excursions permitted between 15°-30°C (59°-86°F)
- use by expiration date on package

Inactive ingredients

anhydrous citric acid, FD&C blue #1, FD&C red #40, flavor, glycerin, high fructose corn syrup, polyethylene glycol 400, propylene glycol, purified water, sodium benzoate, sodium chloride, sodium citrate dihydrate, sodium saccharin, sucralose

Questions or comments?

1-800-426-9391

Principal display panel

LEADER™

NDC 70000-0673-1

Nighttime
Cold & Flu

Acetaminophen
Dextromethorphan HBr
Doxylamine Succinate
Pain Reliever / Fever Reducer
Cough Suppressant
Antihistamine

Cherry
Flavor

Relief of:
• Headache
• Fever
• Sore Throat
• Minor Aches & Pains
• Sneezing
• Runny Nose
• Cough

For Ages 12 & Over

COMPARE TO
VICKS® NYQUIL®
COLD & FLU
active ingredients*

100% Money
Back Guarantee

12 FL OZ (355 mL)

TAMPER EVIDENT: DO NOT USE IF PRINTED
NECK WRAP IS BROKEN OR MISSING

PARENTS:
Learn about teen medicine abuse
www.StopMedicineAbuse.org

*This product is not manufactured or distributed by The Procter &
Gamble Company, owner of the registered trademark Vicks® NyQuil®
Cold & Flu. 50844 ORG032301302

DIST. BY CAH DUBLIN, OH 43017
www.myleader.com
1-800-200-6313

100%
Money Back
Guarantee
Return to place of purchase.

Leader 44-013